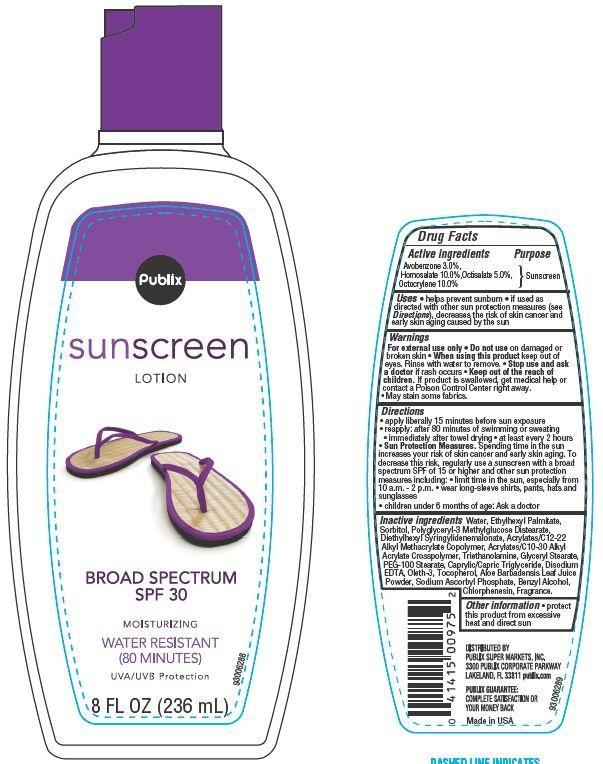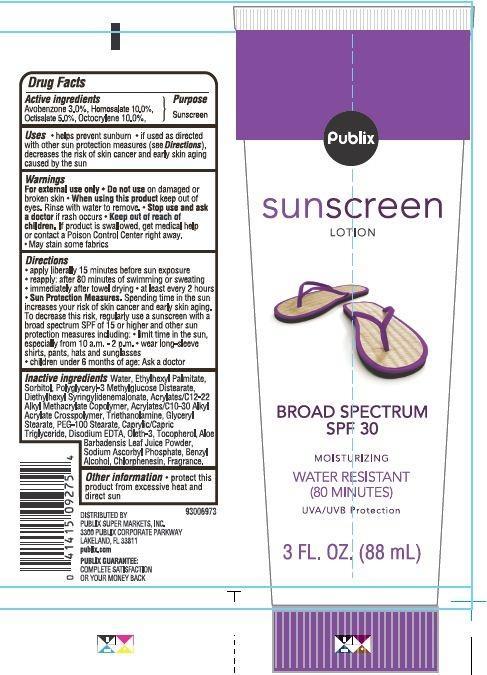 DRUG LABEL: Publix 
NDC: 56062-713 | Form: LOTION
Manufacturer: Publix Super Markets Inc
Category: otc | Type: HUMAN OTC DRUG LABEL
Date: 20130716

ACTIVE INGREDIENTS: AVOBENZONE 3 g/100 g; HOMOSALATE 10 g/100 g; OCTISALATE 5 g/100 g; OCTOCRYLENE 10 g/100 g
INACTIVE INGREDIENTS: WATER; ETHYLHEXYL PALMITATE; SORBITOL; DIETHYLHEXYL SYRINGYLIDENEMALONATE; TROLAMINE; GLYCERYL MONOSTEARATE; EDETATE DISODIUM; PEG-100 STEARATE; TRICAPRYLIN; OLETH-3; TOCOPHEROL; SODIUM ASCORBYL PHOSPHATE; ALOE VERA LEAF; BENZYL ALCOHOL; CHLORPHENESIN

Drug Facts

Active ingredients

Avobenzone 3.0%

Homosalate 10.0%

Octisalate 5.0%

Octocrylene 10.0%

Purpose

Sunscreen

Uses

- helps prevent sunburn
- if used as directed with other sun protection measures (see Directions) decrease the risk of skin cancer and early skin aging caused by sun.

Warnings

For external use only

When using this product

- keep out of eyes. Rinse with water to remove.

Stop use and ask a doctor if

rash occurs

Keep out of the reach of children.

If swallowed get medical help or contact a Poison Control Center right away.

May stain some fabrics

Directions

- apply literally 15 minutes before sun exposure
- reapply: after 80 minutes of swimming or sweating
- immediately after towel drying
- at least every 2 hours

Sun protection measures.

Spending time in the sun increase your risk of skin cancer and early skin

aging. To decrease this risk regularly use a sunscreen with a broad spectrum SPF of 15 or higher and other sun protection measures including:

- Limit time in the sun, especially from 10 am - 2 pm
- Wear long sleeves shirts, pants, hats and sunglasses
- children under 6 month of age: Ask a doctor

Other information

protect this product from excessive heat and direct sun

Inactive ingredients

water, Ethylhexyl Plamitate, Sorbitol, Polyglyceryl-3 Methylglucose Distearate, Diethylhexyl Syringylidenemalonate, Acrylates/C12-22 Alkyl Methacrylate Copolymer, Acrylates/C10-30 Alkyl Acrylate Crosspolymer, Triethanolamine, Glyceryl Stearate, PEG_100 Stearate, Caprylic/Capric Triglyceride,Disodium EDTA, Oleth-3, Tocopherol,Aloe Barbadensis Leaf juice Powder, Sodium Acorbyl Phosphate, Benzyl Alcohol, Chlorphenesin, Fragrance.

Principal Display Panel

publix

SUNSCREEN

LOTION

BROAD SPECTRUM

SPF 30

MOISTURIZING

WATER RESISTlNT

(80 MINTUES)

UVA/UVB Protection

8 FL OZ (236 mL)

publix

SUNSCREEN

LOTION

BROAD SPECTRUM

SPF 30

MOISTURIZING

WATER RESISTlNT

(80 MINTUES)

UVA/UVB Protection

3 FL OZ (88 mL)